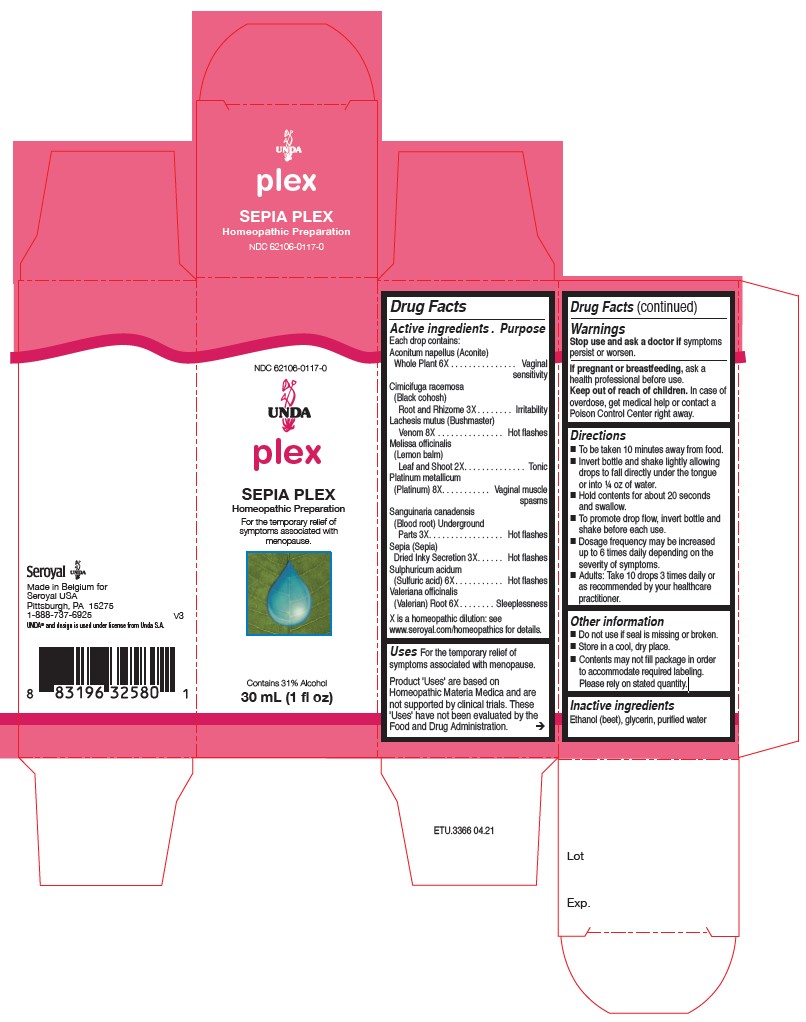 DRUG LABEL: SEPIA PLEX
NDC: 62106-0117 | Form: LIQUID
Manufacturer: Seroyal USA
Category: homeopathic | Type: HUMAN OTC DRUG LABEL
Date: 20210715

ACTIVE INGREDIENTS: BLACK COHOSH 3 [hp_X]/30 mL; LACHESIS MUTA VENOM 8 [hp_X]/30 mL; PLATINUM 8 [hp_X]/30 mL; SANGUINARIA CANADENSIS ROOT 3 [hp_X]/30 mL; SEPIA OFFICINALIS JUICE 3 [hp_X]/30 mL; MELISSA OFFICINALIS 2 [hp_X]/30 mL; SULFURIC ACID 6 [hp_X]/30 mL; VALERIAN 6 [hp_X]/30 mL; ACONITUM NAPELLUS 6 [hp_X]/30 mL
INACTIVE INGREDIENTS: ALCOHOL; WATER; GLYCERIN

SEPIA PLEX

Active ingredients
Each drop contains:
Aconitum napellus (Aconite) Whole Plant 6X
Cimicifuga racemosa (Black cohosh) Root and Rhizome 3X
Lachesis mutus (Bushmaster) Venom 8X
Melissa officinalis (Lemon balm) Leaf and Shoot 2X
Platinum metallicum (Platinum) 8X
Sanguinaria canadensis (Blood root) Underground Parts 3X
Sepia Dried Inky Secretion 3X
Sulphuricum acidum (Sulfuric acid) 6X
Valeriana officinalis (Valerian) Root 6X

Uses

For the temporary relief of symptoms associated with menopause.

Warnings
Stop use and ask a doctor if symptoms persist or worsen.
If pregnant or breastfeeding, ask a health professional before use.
Keep out of reach of children. In case of overdose, get medical help or contact a
Poison Control Center right away.

Keep out of reach of children. In case of
overdose, get medical help or contact a
Poison Control Center right away.

PREGNANCY OR BREAST FEEDING

If pregnant or breastfeeding, ask a
health professional before use.

Other information
Do not use if seal is missing or broken.
Store in a cool, dry place.

Contents may not fill package in order
to accommodate required labeling.
Please rely on stated quantity.

Inactive ingredients
Ethanol (beet), glycerin, purified water

Directions
To be taken ten minutes away from food.
Invert bottle and shake lightly allowing
drops to fall directly under the tongue
or into ¼ oz of water.
Hold contents for about 20 seconds
and swallow.
To promote drop flow, invert bottle and
shake before each use.

Dosage frequency may be increased
up to six times daily depending on the
severity of symptoms.
Adults: Take 10 drops three times daily
or as recommended by your healthcare
practitioner.

Uses

For the temporary relief of symptoms associated with menopause.

Directions
To be taken ten minutes away from food.

Invert bottle and shake lightly allowing
drops to fall directly under the tongue
or into ¼ oz of water.
Hold contents for about 20 seconds
and swallow.
To promote drop flow, invert bottle and
shake before each use.
Dosage frequency may be increased
up to six times daily depending on the
severity of symptoms.
Adults: Take 10 drops three times daily
or as recommended by your healthcare
practitioner.

PACKAGE LABEL

NDC 62106-0117-0

UNDA

plex

SEPIA PLEX

Homeopathic Preparation

For the temporary relief of symptoms associated with menopause.

Contains 31% Alcohol

1 fl oz (30 mL)